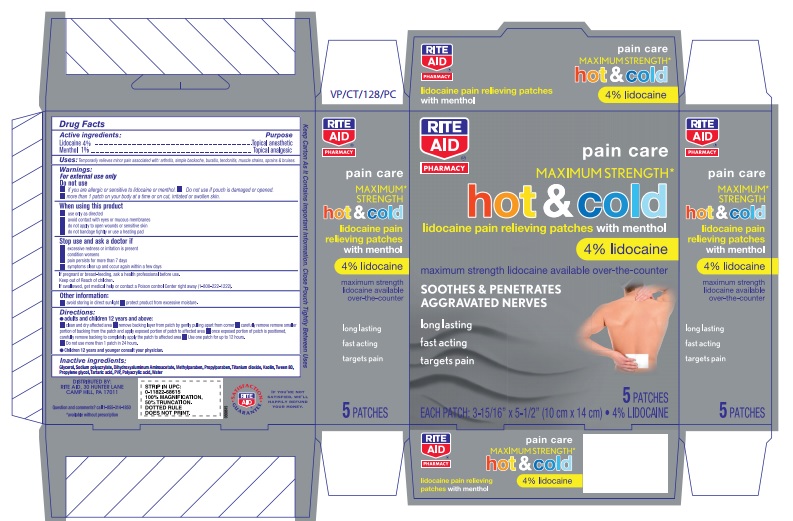 DRUG LABEL: Hot and Cold Lidocaine with Menthol Patch
NDC: 76168-304 | Form: PATCH
Manufacturer: Velocity Pharma LLC
Category: otc | Type: HUMAN OTC DRUG LABEL
Date: 20170920

ACTIVE INGREDIENTS: LIDOCAINE 40 mg/1 1; MENTHOL 10 mg/1 1
INACTIVE INGREDIENTS: POVIDONE; TARTARIC ACID; WATER; KAOLIN; POLYSORBATE 80; POLYACRYLIC ACID (250000 MW); SILICON DIOXIDE; SODIUM POLYACRYLATE (2500000 MW); TITANIUM DIOXIDE; DIHYDROXYALUMINUM AMINOACETATE; GLYCERIN; METHYLPARABEN; PROPYLENE GLYCOL; PROPYLPARABEN

Hot and Cold Lidocaine with Menthol Patch- RA

Drug Facts

ACTIVE INGREDIENT

Active Ingredients | Purpose
Lidocaine 4 % | Topical analgesic
Menthol 1% | Topical analgesic

Uses

Temporarily relieves minor pain associated with: arthritis, simple backache, bursitis, tendonitis, muscle strains, sprains & bruises.

Warnings

For external use only.

Do not use if you are allergic or sensitive to lidocaine or menthol. Do not use if pouch is damaged or opened.

When using this product

- use only as directed
- avoid contact with eyes or mucous membranes
- do not apply to open wounds or sensitive skin
- do not bandage tightly or use a heating pad

Stop use and ask a doctor if

- excessive redness or irritation is present
- condition worsens
- pain persists for more than 7 days
- symptoms clear up and occur again within a few days

PREGNANCY OR BREAST FEEDING

If pregnant or breast-feeding, ask a health professional before use.

Keep out of Reach of children. If swallowed, get medical help or contact a Poison control Center right away.

Directions

- adults: apply patch to affected area for a maximum of 12 hours. Do not use more than 1 patch every 24 hours.
- children: consult your physician
- remove protective film, gently apply to affected area.

Inactive Ingredients

Dihydroxyaluminium aminoacetate, Glycerol, Kaolin, Methylparaben, Polyacrylic acid, Propylene glycol, Propylparaben, PVP, Sodium polyacrylate, Tartaric acidm Titanium diocide, Tween 80, Water

PRINCIPAL DISPLAY PANEL

CONTAINS LIDOCAINE with Menthol- RA

PAIN RELIEF PATCH

5TOPICAL PATCHES PER BOX